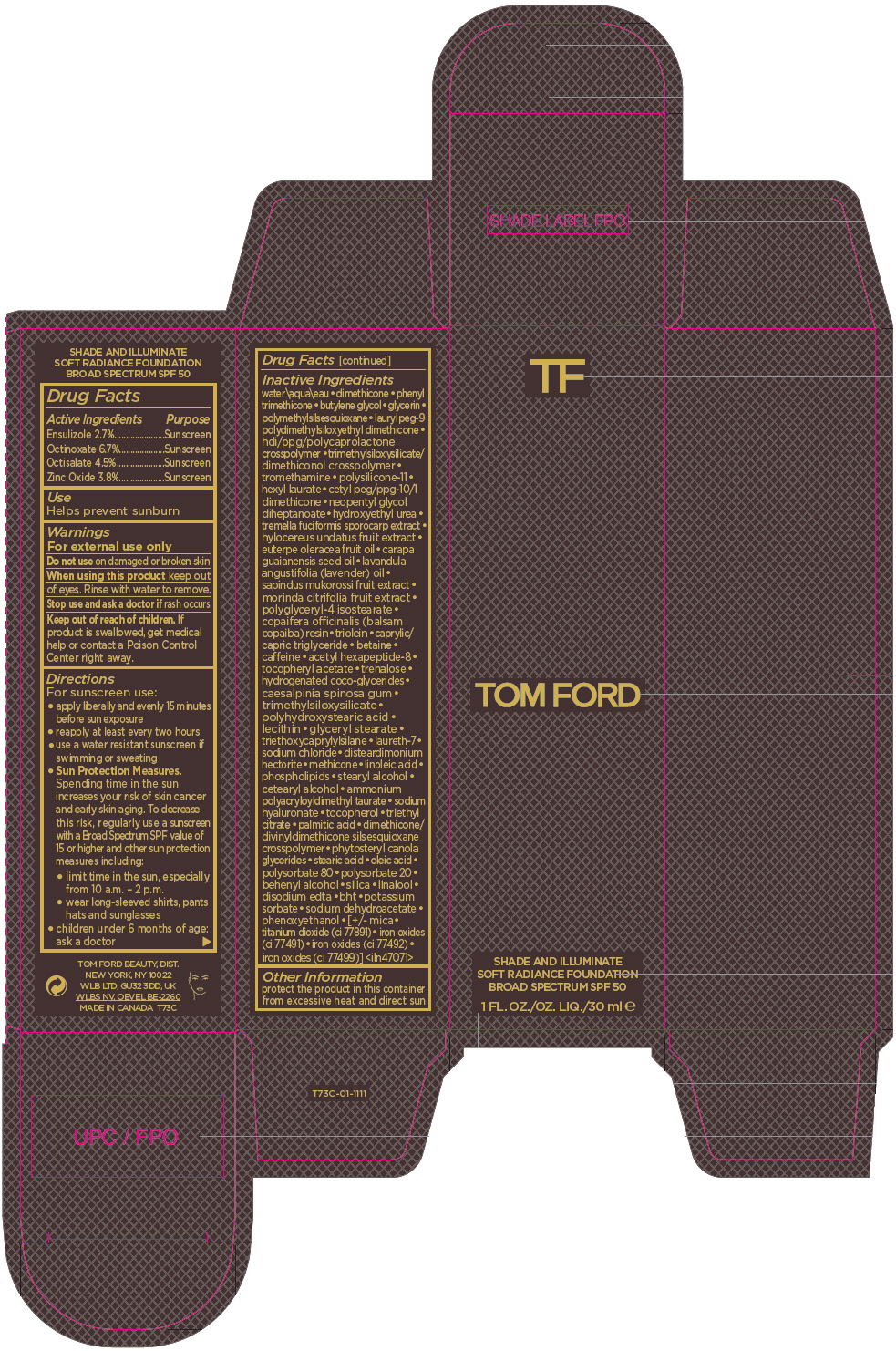 DRUG LABEL: TOM FORD SHADE AND ILLUMINATE SOFT RADIANCE FOUNDATION BROAD SPECTRUM SPF 50
NDC: 76398-010 | Form: LIQUID
Manufacturer: TOM FORD BEAUTY DIST
Category: otc | Type: HUMAN OTC DRUG LABEL
Date: 20231005

ACTIVE INGREDIENTS: ENSULIZOLE 27 mg/1 mL; OCTINOXATE 67 mg/1 mL; OCTISALATE 45 mg/1 mL; ZINC OXIDE 38 mg/1 mL
INACTIVE INGREDIENTS: WATER; DIMETHICONE; PHENYL TRIMETHICONE; BUTYLENE GLYCOL; GLYCERIN; POLYMETHYLSILSESQUIOXANE (4.5 MICRONS); LAURYL PEG-9 POLYDIMETHYLSILOXYETHYL DIMETHICONE; TROMETHAMINE; DIMETHICONE/VINYL DIMETHICONE CROSSPOLYMER (SOFT PARTICLE); HEXYL LAURATE; NEOPENTYL GLYCOL DIHEPTANOATE; HYDROXYETHYL UREA; TREMELLA FUCIFORMIS FRUITING BODY; SELENICEREUS UNDATUS FRUIT; ACAI OIL; CARAPA GUIANENSIS SEED OIL; LAVENDER OIL; SAPINDUS MUKOROSSI FRUIT; NONI FRUIT; POLYGLYCERYL-4 ISOSTEARATE; COPAIFERA OFFICINALIS RESIN; GLYCERYL TRIOLEATE; MEDIUM-CHAIN TRIGLYCERIDES; BETAINE; CAFFEINE; ACETYL HEXAPEPTIDE-8; .ALPHA.-TOCOPHEROL ACETATE; TREHALOSE; HYDROGENATED COCO-GLYCERIDES; CAESALPINIA SPINOSA RESIN; GLYCERYL MONOSTEARATE; TRIETHOXYCAPRYLYLSILANE; LAURETH-7; SODIUM CHLORIDE; DISTEARDIMONIUM HECTORITE; METHICONE (20 CST); LINOLEIC ACID; LECITHIN, SOYBEAN; STEARYL ALCOHOL; CETOSTEARYL ALCOHOL; AMMONIUM POLYACRYLOYLDIMETHYL TAURATE (55000 MPA.S); HYALURONATE SODIUM; TOCOPHEROL; TRIETHYL CITRATE; PALMITIC ACID; STEARIC ACID; OLEIC ACID; POLYSORBATE 80; POLYSORBATE 20; DOCOSANOL; SILICON DIOXIDE; LINALOOL, (+/-)-; EDETATE DISODIUM ANHYDROUS; BUTYLATED HYDROXYTOLUENE; POTASSIUM SORBATE; SODIUM DEHYDROACETATE; PHENOXYETHANOL; MICA; TITANIUM DIOXIDE; FERRIC OXIDE RED; FERRIC OXIDE YELLOW; FERROSOFERRIC OXIDE

TOM FORD SHADE AND ILLUMINATE SOFT RADIANCE FOUNDATION BROAD SPECTRUM SPF 50

Drug Facts

ACTIVE INGREDIENT

Active Ingredients | Purpose
Ensulizole 2.7% | Sunscreen
Octinoxate 6.7% | Sunscreen
Octisalate 4.5% | Sunscreen
Zinc Oxide 3.8% | Sunscreen

Use

Helps prevent sunburn

Warnings

For external use only

Do not use on damaged or broken skin

When using this product keep out of eyes. Rinse with water to remove.

Stop use and ask a doctor if rash occurs

Keep out of reach of children. If product is swallowed, get medical help or contact a Poison Control Center right away.

Directions

For sunscreen use:

- apply liberally and evenly 15 minutes before sun exposure
- reapply at least every two hours
- use a water resistant sunscreen if swimming or sweating
- Sun Protection Measures. Spending time in the sun increases your risk of skin cancer and early skin aging. To decrease this risk, regularly use a sunscreen with a Broad Spectrum SPF value of 15 or higher and other sun protection measures including:
  - limit time in the sun, especially from 10 a.m. – 2 p.m.
  - wear long-sleeved shirts, pants hats and sunglasses
- children under 6 months of age: ask a doctor

Inactive Ingredients

water\aqua\eau • dimethicone • phenyl trimethicone • butylene glycol • glycerin • polymethylsilsesquioxane • lauryl peg-9 polydimethylsiloxyethyl dimethicone • hdi/ppg/polycaprolactone crosspolymer • trimethylsiloxysilicate/dimethiconol crosspolymer • tromethamine • polysilicone-11 • hexyl laurate • cetyl peg/ppg-10/1 dimethicone • neopentyl glycol diheptanoate • hydroxyethyl urea • tremella fuciformis sporocarp extract • hylocereus undatus fruit extract • euterpe oleracea fruit oil • carapa guaianensis seed oil • lavandula angustifolia (lavender) oil • sapindus mukorossi fruit extract • morinda citrifolia fruit extract • polyglyceryl-4 isostearate • copaifera officinalis (balsam copaiba) resin • triolein • caprylic/capric triglyceride • betaine • caffeine • acetyl hexapeptide-8 • tocopheryl acetate • trehalose • hydrogenated coco-glycerides • caesalpinia spinosa gum • trimethylsiloxysilicate • polyhydroxystearic acid • lecithin • glyceryl stearate • triethoxycaprylylsilane • laureth-7 • sodium chloride • disteardimonium hectorite • methicone • linoleic acid • phospholipids • stearyl alcohol • cetearyl alcohol • ammonium polyacryloyldimethyl taurate • sodium hyaluronate • tocopherol • triethyl citrate • palmitic acid • dimethicone/divinyldimethicone silsesquioxane crosspolymer • phytosteryl canola glycerides • stearic acid • oleic acid • polysorbate 80 • polysorbate 20 • behenyl alcohol • silica • linalool • disodium edta • bht • potassium sorbate • sodium dehydroacetate • phenoxyethanol • [+/- mica • titanium dioxide (ci 77891) • iron oxides (ci 77491) • iron oxides (ci 77492) • iron oxides (ci 77499)] <iln47071>

Other Information

protect the product in this container from excessive heat and direct sun

PRINCIPAL DISPLAY PANEL - 30 mL Bottle Carton

TOM FORD

SHADE AND ILLUMINATE
SOFT RADIANCE FOUNDATION
BROAD SPECTRUM SPF 50

1 FL. OZ./OZ. LIQ./30 ml ℮